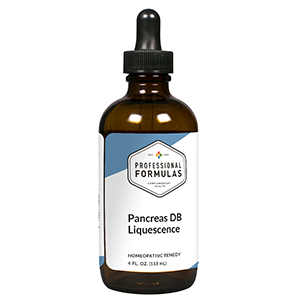 DRUG LABEL: Pancreas DB Liquescence
NDC: 63083-3037 | Form: LIQUID
Manufacturer: Professional Complementary Health Formulas
Category: homeopathic | Type: HUMAN OTC DRUG LABEL
Date: 20190815

ACTIVE INGREDIENTS: TRILLIUM ERECTUM ROOT 1 [hp_X]/118 mL; FENUGREEK SEED 3 [hp_X]/118 mL; GYMNEMA SYLVESTRE LEAF 3 [hp_X]/118 mL; PHOSPHORIC ACID 3 [hp_X]/118 mL; RHUS AROMATICA ROOT BARK 3 [hp_X]/118 mL; SYZYGIUM CUMINI SEED 3 [hp_X]/118 mL; SILVER NITRATE 6 [hp_X]/118 mL; CHIONANTHUS VIRGINICUS BARK 6 [hp_X]/118 mL; PHOSPHORUS 6 [hp_X]/118 mL; ZINC 6 [hp_X]/118 mL; BOS TAURUS PANCREAS 6 [hp_X]/118 mL; CHROMIUM 8 [hp_X]/118 mL; SULFUR 8 [hp_X]/118 mL; VANADIUM 8 [hp_X]/118 mL; LYCOPODIUM CLAVATUM SPORE 8 [hp_X]/118 mL; HEXAPLEX TRUNCULUS HYPOBRANCHIAL GLAND JUICE 12 [hp_X]/118 mL; INSULIN GLULISINE 30 [hp_X]/118 mL; URANYL NITRATE HEXAHYDRATE 30 [hp_X]/118 mL
INACTIVE INGREDIENTS: ALCOHOL; WATER

T37

ACTIVE INGREDIENTS

Trillium pendulum 1X
Fenugreek 3X
Gymnema 3X
Phosphoricum acidum 3X
Rhus aromatica 3X
Syzygium jambolanum 3X
Argentum nitricum 6X
Chionanthus virginica 6X
Phosphorus 6X
Zincum metallicum 6X
Pancreas 6X, 8X
Chromium 8X
Sulphur 8X
Vanadium metallicum 8X
Lycopodium clavatum 8X, 30X
Murex purpurea 12X
DNA insulin 30X
Uranium nitricum 30X

QUESTIONS

Professional Formulas

PO Box 2034 Lake Oswego, OR 97035

INDICATIONS

For the temporary relief of mild abdominal pain or tenderness, muscle pain, cramps, or weakness, loss of appetite, weight loss, diarrhea, nausea, or vomiting.*

PURPOSE

*Claims based on traditional homeopathic practice, not accepted medical evidence. Not FDA evaluated.

WARNINGS

Severe or persistent symptoms may be serious. Consult a doctor promptly. Keep out of the reach of children. In case of overdose, get medical help or contact a poison control center right away. If pregnant or breastfeeding, ask a healthcare professional before use.

Keep out of the reach of children.

PREGNANCY OR BREAST FEEDING

If pregnant or breastfeeding, ask a healthcare professional before use.

DIRECTIONS

Place drops under tongue 30 minutes before/after meals. Adults and children 12 years and over: Take one full dropper up to 2 times per day. Consult a physician for use in children under 12 years of age.

OTHER INFORMATION

Tamper resistant. If seal is broken, do not use. After opening, close container tightly and store at room temperature away from heat.

INACTIVE INGREDIENTS

20% ethanol, purified water.

LABEL

Est 1985

Professional Formulas

Complementary Health

Pancreas DB Liquescence

Homeopathic Remedy

4 FL. OZ. (118 mL)